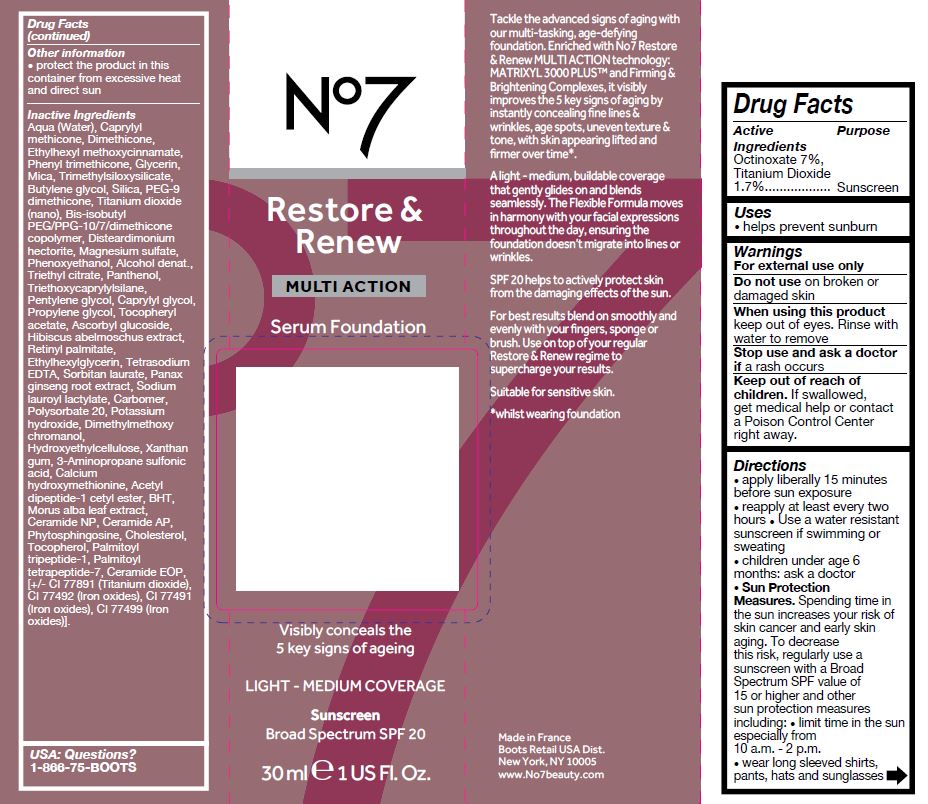 DRUG LABEL: No7 Restore and Renew Multi Action Serum Foundation Sunscreen Broad Spectrum SPF 20 Bamboo
NDC: 61589-9537 | Form: CREAM
Manufacturer: BCM Cosmetique SAS
Category: otc | Type: HUMAN OTC DRUG LABEL
Date: 20260205

ACTIVE INGREDIENTS: OCTINOXATE 2.1 g/30 g; TITANIUM DIOXIDE 0.51 g/30 g
INACTIVE INGREDIENTS: WATER; CAPRYLYL TRISILOXANE; GLYCERIN; MICA; DIMETHICONE; BUTYLENE GLYCOL; PEG-9 DIMETHICONE; TRIMETHYLSILOXYSILICATE (M/Q 0.6-0.8); DISTEARDIMONIUM HECTORITE; MAGNESIUM SULFATE, UNSPECIFIED; PHENOXYETHANOL; .ALPHA.-TOCOPHEROL ACETATE; PROPYLENE GLYCOL; TRIETHOXYCAPRYLYLSILANE; PENTYLENE GLYCOL; ASCORBYL GLUCOSIDE; PANAX GINSENG ROOT WATER; CARBOMER 940; DIMETHYLMETHOXY CHROMANOL; POTASSIUM HYDROXIDE; POLYSORBATE 20; XANTHAN GUM; TOCOPHEROL; N-ACETYL DIPEPTIDE-1; VITAMIN A PALMITATE; MORUS ALBA LEAF; ETIDRONATE TETRASODIUM; PALMITOYL TRIPEPTIDE-1; PALMITOYL TETRAPEPTIDE-7; PHENYL TRIMETHICONE; SILICON DIOXIDE; PEG/PPG-10/2 DIMETHICONE; ALCOHOL; TRIETHYL CITRATE; PANTHENOL; CAPRYLYL GLYCOL; ABELMOSCHUS MOSCHATUS FLOWER; ETHYLHEXYLGLYCERIN; SORBITAN MONOLAURATE; SODIUM LAUROYL LACTYLATE; HYDROXYETHYL CELLULOSE, UNSPECIFIED; N-TRIS((HYDROXYMETHYL)METHYL)-3-AMINOPROPANESULFONIC ACID; DESMENINOL CALCIUM; BUTYLATED HYDROXYTOLUENE; CERAMIDE 3; CERAMIDE AP; PHYTOSPHINGOSINE; CHOLESTEROL; CERAMIDE 9; FERRIC OXIDE YELLOW; FERRIC OXIDE RED; FERROSOFERRIC OXIDE

No7 Restore and Renew Multi Action Serum Foundation Sunscreen Broad Spectrum SPF 20 Bamboo

Carton Active Ingredients Section

Active Ingredients

Octinoxate 7% Titanium dioxide 1.7%

Uses

Uses - helps prevent sunburn

Warnings

For external use only

Do not use on damaged or broken skin

When using this product keep out of eyes. Rinse with water to remove

Warnings

For external use only

Do not use on damaged or broken skin

When using this product keep out of eyes. Rinse with water to remove

Ask a doctor

Stop use and ask a doctor if rash occurs.

Keep out of reach of children. If swallowed, get medical help or contact a Poison Control Center right away.

Directions

Directions for suncreen use

apply liberally 15 minutes before sun exposure

reapply at least every 2 hours

use a water resistant sunscreen if swimming or sweating

children under 6 months of age: Ask a doctor

Sun Protection Measures. Spending time in the sun increases your risk of skin cancer and early skin aging. To decrease this risk, regularly use a sunscreen with a Broad Spectrum SPF value of 15 or higher and other sun protection measures including:

limit time in the sun, especially from 10 a.m. - 2 p.m.

wear long-sleeved shirts, pants, hats, and sunglasses

Directions

Directions for suncreen use

apply liberally 15 minutes before sun exposure

reapply at least every 2 hours

use a water resistant sunscreen if swimming or sweating

children under 6 months of age: Ask a doctor

Sun Protection Measures. Spending time in the sun increases your risk of skin cancer and early skin aging. To decrease this risk, regularly use a sunscreen with a Broad Spectrum SPF value of 15 or higher and other sun protection measures including:

limit time in the sun, especially from 10 a.m. - 2 p.m.

wear long-sleeved shirts, pants, hats, and sunglasses

Other information

Protect the product in this container from excessive heat and direct sun

Inactive ingredients

Aqua (Water), Caprylyl methicone, Dimethicone, Ethylhexyl methoxycinnamate, Phenyl trimethicone, Glycerin, Mica, trimethylsiloxysilicate, Butylene glycol, Silica, PEG-9 dimethicone, Titanium dioxide (nano), Bis-isobutyl PEF/PPG-10/7/dimethicone copolymer, Disteardimonium hectorite, Magnesium sulfate, Phenoxyethanol, Alcohol denate., Triethyl citrate, Panthenol, Triethoxycaprylylsilane, Pentylene glycol, Caprylyl glycol, Propylene glycol, Tocopheryl acetate, Ascorbyl glucoside, Hibiscus abelmoschus extract, Retinyl palmitate, Ethylhexylglycerin, Tetrasodium EDTA, Sorbitan laurate, Panax ginseng root extract, Sodium lauroyl lactylate, Carbomer, Polysorbate 20, Potassium hydroxide, Dimethylmethoxy chromanol, Hydroxyethylcellulose, Xanthan gum, 3-Aminopropane sulfonic acid, Calcium hydroxymethionine, Acetyl dipeptide-1 cetyl ester, BHT, Morus alba leaf extract, Ceramide NP, Ceramide AP, Phytosphingosine, Cholesterol, Tocopherol, Palmitoyl tripeptide-1, Palmitoyl tetrapeptide-7, Ceramide EOP, [+/- CI 77891 (Titanium dioxide), CI 77492 (Iron oxides), CI 77491 (Iron oxides), CI 77499 (Iron oxides)].

DESCRIPTION

No7

Restore & Renew

MULTI ACTION

Serum Foundation

Visibly conceals the 5 key signs of ageing

LIGHT - MEDIUM COVERAGE

30 ml e 1 US Fl. Oz.

Tackle the advanced signs of aging with our multi-tasking, age-defying foundation. Enriched with No7 Restore & Renew MULTI ACTION technology: MATRIXYL 3000 PLUS and Firming & Brightening Complexes, it visibly improves the 5 key signs of aging by instantly concealing fine lines & wrinkles, age spots, uneven texture & tone, with skin appearing lifted and firmer over time*.

A light - medium, buildable coverage that gently glides on and blends seamlessly. The Flexible Formula moves in harmony with your facial expressions throughout the day, ensuring the foundation doesn't migrate into lnes or wrinkles.

SPF 20 helps to actively protect skin from the damaging effects of the sun.

For best results blend on smoothyl and evenly with your fingers, sponge or brush. Use on top of your regular Restore & Renew regime to superchage your results.

Suitable for sensitive skin.

*whilst wearing foundation

Information

Made in France

Boots Retail USA Dist.

New York, NY 10005

www.No7beauty.com